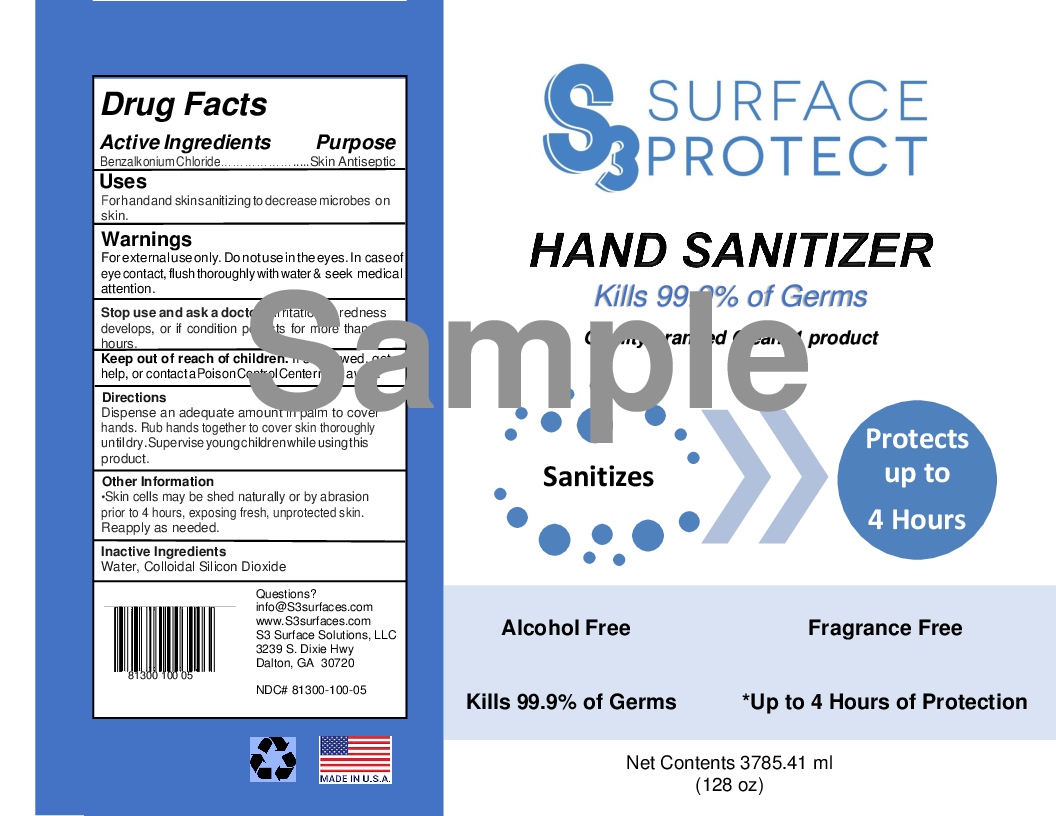 DRUG LABEL: Clean31
NDC: 81300-100 | Form: LIQUID
Manufacturer: S3 Surface Solutions, LLC
Category: otc | Type: HUMAN OTC DRUG LABEL
Date: 20210107

ACTIVE INGREDIENTS: BENZALKONIUM CHLORIDE 0.13 g/100 mL
INACTIVE INGREDIENTS: WATER 99.67 g/100 mL; SILICON DIOXIDE 0.2 g/100 mL

Active Ingredients

Benzalkonium Chloride 0.13%

Purpose

Skin Anticeptic

Uses

For hand and skin sanitizing to decrease microbes on skin

Warnings

For external use only. Do not use in the eyes. In case of eye contact, flush thoroughly with water & seek medical attention

Stop use and ask a doctor

If irritation or redness develops, or if condition persists for more than 72 hours

Keep out of reach of Children

If swallowed, get medical help or contact a Poison Control Center right away.

Directions

Dispense an adequate amount in palm to cover hands. Rub hands together to cover skin thoroughly until dry. Supervise young children while using this product.

Other Information

Skin cells may be shed naturally or by abrasion prior to 4 hours, exposing fresh, unprotected skin. Reapply as needed.

Inactive Ingredients

Water, Colloidal Silicon Dioxide

Questions?

email info@S3Surfaces.com

Alcohol-Free Formulation

S3 Surface Protect, Quality branded Clean31 Protection, Hand Sanitizer, Sanitizes, Protects up to 4 hours, Alcohol-Free, Fragrance-free, Up to 4 hours of Protection, Kills over 99.9% of Germs

Hand Sanitizer Label

Product label picture